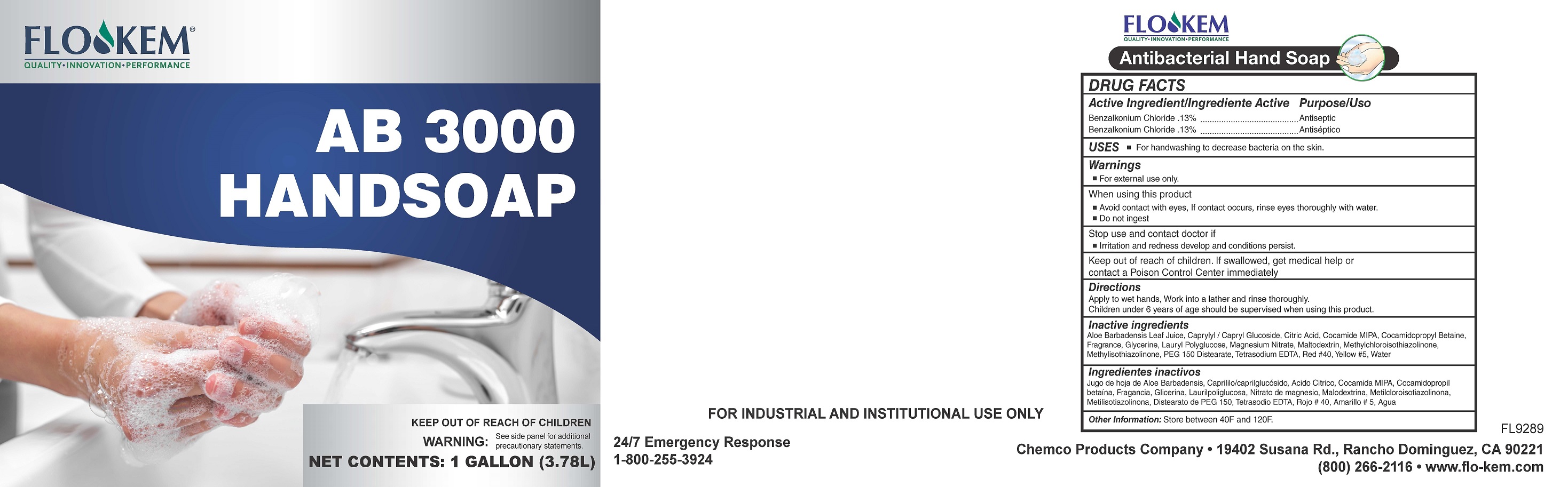 DRUG LABEL: AB 3000
NDC: 63039-1006 | Form: LIQUID
Manufacturer: Chemco
Category: otc | Type: HUMAN OTC DRUG LABEL
Date: 20251106

ACTIVE INGREDIENTS: BENZALKONIUM CHLORIDE 0.13 kg/100 kg
INACTIVE INGREDIENTS: ALOE VERA LEAF; CAPRYLYL/CAPRYL OLIGOGLUCOSIDE; ANHYDROUS CITRIC ACID; COCO MONOISOPROPANOLAMIDE; COCAMIDOPROPYL BETAINE; GLYCERIN; LAURYL GLUCOSIDE; MAGNESIUM NITRATE; MALTODEXTRIN; METHYLCHLOROISOTHIAZOLINONE; METHYLISOTHIAZOLINONE; PEG-150 DISTEARATE; FD&C RED NO. 40; EDETATE SODIUM; WATER; FD&C YELLOW NO. 5

AB 3000 Hand Soap

ACTIVE INGREDIENT

Benzalkonium Chloride...........0.13%

Inactive Ingredients

Aloe Barbadensis Leaf Juice, Benzisothiazolinone, Caprylyl Glucoside, Citric Acid, Cocamide MIPA, Cocamidopropyl Betaine, Fragrance, Glycerine, Lauryl Glucoside, Maltodextrin, Methylisothiozolinone, PEG 150 Distearate, Red #40, Tetrasodium EDTA, Water, Yellow #5

Purpose

Antibacterial

Uses

For hand washing to decrease bacteria on the skin.

Warnings

For external use only.

When Using this Product

Avoid contact with eyes. If contat occurs, rinse eyes thoroughly with water.

Do not ingest. Stop use and contact a doctor if irritation and

redness develop and conditions persist.

Keep out of reach of children.

If swallowed, get medical help

or contact Poison Control Center immediately.

Directions

- Apply to wet hands. Work into lather and rinse thoroughly.

- Children under 6 years of age should be supervised when using this product.